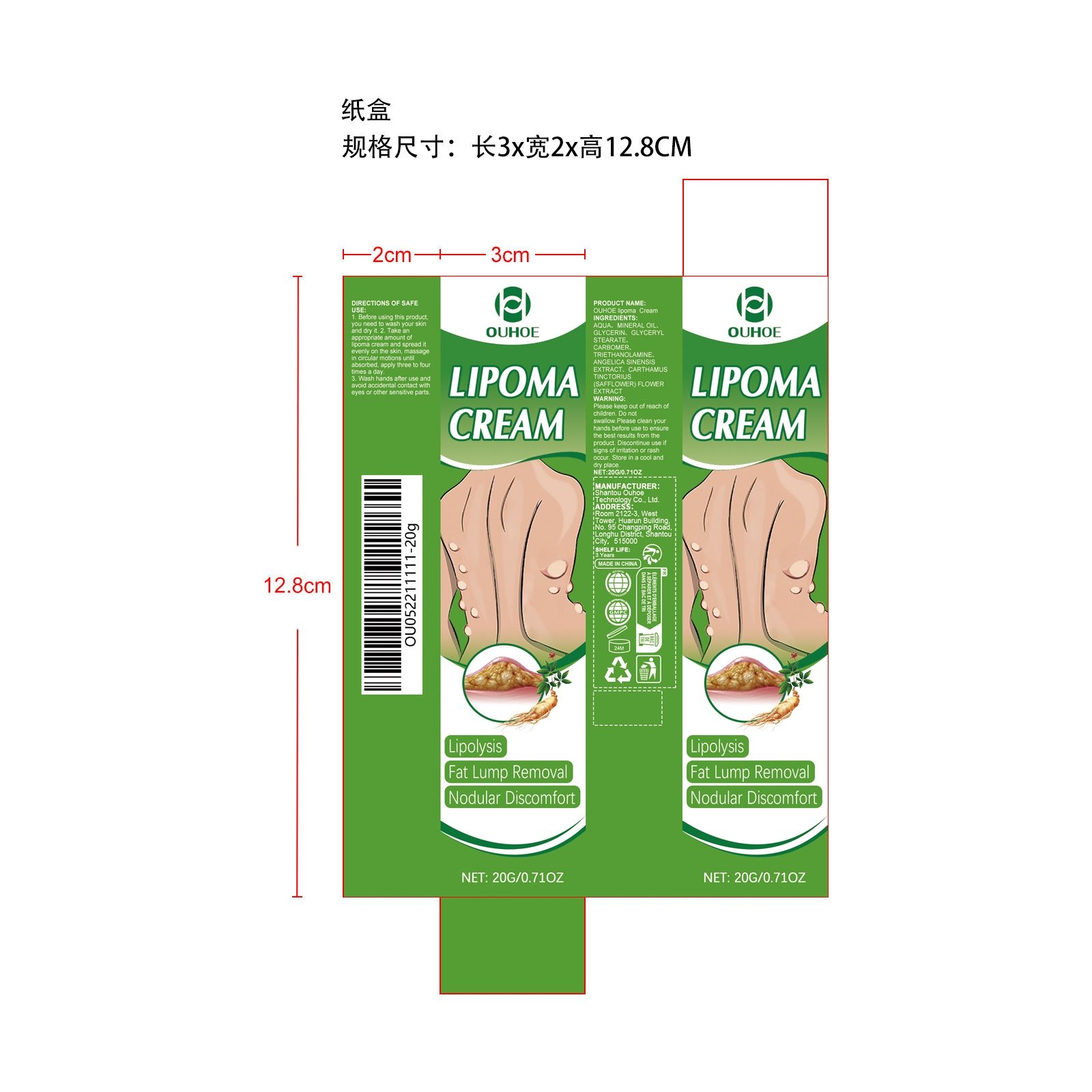 DRUG LABEL: OUHOE Lipoma Cream
NDC: 85163-007 | Form: CREAM
Manufacturer: Shantou Ouhoe Technology Co., Ltd.
Category: otc | Type: HUMAN OTC DRUG LABEL
Date: 20251127

ACTIVE INGREDIENTS: ANGELICA SINENSIS ROOT 0.004 mg/20 mg; CARTHAMUS TINCTORIUS (SAFFLOWER) FLOWER 0.004 mg/20 mg
INACTIVE INGREDIENTS: MINERAL OIL 2 mg/20 mg; GLYCERIN 1.6 mg/20 mg; GLYCERYL STEARATE 0.4 mg/20 mg; CARBOMER 0.04 mg/20 mg; AQUA 15.912 mg/20 mg; TRIETHANOLAMINE 0.04 mg/20 mg

ACTIVE INGREDIENT

ANGELICA SINENSIS EXTRACT、CARTHAMUS TINCTORIUS (SAFFLOWER) FLOWER EXTRACT

PURPOSE

Lipolysis、Fat Lump Removal、Nodular Discomfort

WHEN USING

1. Before using this product, you need to wash your skin and dry it.

2. Take an appropriate amount of lipoma cream and spread it evenly on the skin, massage in circular motions until absorbed, apply three to four times a day.

3. Wash hands after use and avoid accidental contact with eyes or other sensitive parts.

WARNINGS

Please keep out of reach of children. Do not swallow.Please clean your hands before use to ensure the best results from the product. Discontinue use if signs of irritation or rash occur. Store in a cool and dry place.

DO NOT USE

Discontinue use if signs of irritation or rash occur.

STOP USE

Discontinue use if signs of irritation or rash occur.

KEEP OUT OF REACH OF CHILDREN

Please keep out of reach of children. Do not swallow.

STORAGE AND HANDLING

Store in a cool and dry place.

INACTIVE INGREDIENT

AQUA、MINERAL OIL、GLYCERIN、GLYCERYL STEARATE、CARBOMER、TRIETHANOLAMINE

DOSAGE AND ADMINISTRATION

Take an appropriate amount of lipoma cream and spread it evenly on the skin, massage in circular motions until absorbed, apply three to four times a day.

INDICATIONS AND USAGE

Lipolysis
Fat Lump Removal
Nodular Discomfort